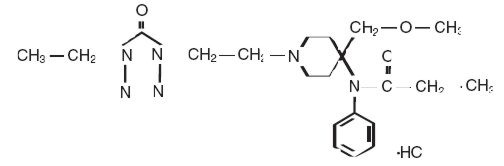 DRUG LABEL: Unknown
Manufacturer: TAYLOR PHARMACEUTICALS
Category: prescription | Type: HUMAN PRESCRIPTION DRUG LABELING
Date: 20080225
DEA Schedule: CII

ALFENTA®

CII

Rx only

DESCRIPTION

ALFENTA (alfentanil hydrochloride) Injection is an opioid analgesic chemically designated as N-[1-[2-(4-ethyl-4,5-dihydro-5-oxo-1H-tetrazol-1-yl)ethyl]-4-(methoxymethyl)-4-piperidinyl]-N-phenylpropanamide monohydrochloride (1:1) with a molecular weight of 452.98 and an n-octanol:water partition coefficient of 128:1 at pH 7.4. The structural formula of ALFENTA is:

ALFENTA is a sterile, non-pyrogenic, preservative free aqueous solution containing alfentanil hydrochloride equivalent to 500 µg per mL of alfentanil base for intravenous injection. The solution, which contains sodium chloride for isotonicity, has a pH range of 4-6. Each mL contains: Active: Alfentanil base 500 mcg. Inactive: Sodium Chloride 9 mg and Water for Injection Q.S.

CLINICAL PHARMACOLOGY

ALFENTA (alfentanil hydrochloride) is an opioid analgesic with a rapid onset of action.

At doses of 8-40 mcg/kg for surgical procedures lasting up to 30 minutes, ALFENTA provides analgesic protection against hemodynamic responses to surgical stress with recovery times generally comparable to those seen with equipotent fentanyl dosages.

For longer procedures, doses of up to 75 mcg/kg attenuate hemodynamic responses to laryngoscopy, intubation and incision, with recovery time comparable to fentanyl. At doses of 50-75 mcg/kg followed by a continuous infusion of 0.5-3 mcg/kg/min, ALFENTA attenuates the catecholamine response with more rapid recovery and reduced need for postoperative analgesics as compared to patients administered enflurane. At doses of 5 mcg/kg, ALFENTA provides analgesia for the conscious but sedated patient. Based on patient response, doses higher than 5 mcg/kg may be needed. Elderly or debilitated patients may require lower doses. High intrasubject and intersubject variability in the pharmacokinetic disposition of ALFENTA has been reported.

The pharmacokinetics of ALFENTA can be described as a three-compartment model with sequential distribution half-lives of 1 and 14 minutes; and a terminal elimination half-life of 90-111 minutes (as compared to a terminal elimination half-life of approximately 475 minutes for fentanyl and approximately 265 minutes for sufentanil at doses of 250 mcg). The liver is the major site of biotransformation.

ALFENTA has an apparent volume of distribution of 0.4-1 L/kg, which is approximately one-fourth to one-tenth that of fentanyl, with an average plasma clearance of 5 mL/kg/min as compared to approximately 8 mL/kg/min for fentanyl.

Only 1.0% of the dose is excreted as unchanged drug; urinary excretion is the major route of elimination of metabolites. Plasma protein binding of ALFENTA is approximately 92%.

In one study involving 15 patients administered ALFENTA with nitrous oxide/oxygen, a narrow range of plasma ALFENTA concentrations, approximately 310-340 ng/mL, was shown to provide adequate anesthesia for intra-abdominal surgery, while lower concentrations, approximately 190 ng/mL, blocked responses to skin closure. Plasma concentrations between 100-200 ng/mL provided adequate anesthesia for superficial surgery.

ALFENTA has an immediate onset of action. At dosages of approximately 105 mcg/kg, ALFENTA produces hypnosis as determined by EEG patterns; an anesthetic ED90 of 182 mcg/kg for ALFENTA in unpremedicated patients has been determined, based upon the ability to block response to placement of a nasopharyngeal airway. Based on clinical trials, induction dosage requirements range from 130-245 mcg/kg. For procedures lasting 30-60 minutes, loading dosages of up to 50 mcg/kg produce the hemodynamic response to endotracheal intubation and skin incision as comparable to those from fentanyl. A pre-intubation loading dose of 50-75 mcg/kg prior to a continuous infusion attenuates the response to laryngoscopy, intubation and incision. Subsequent administration of ALFENTA infusion administered at a rate of 0.5-3 mcg/kg/min with nitrous oxide/oxygen attenuates sympathetic responses to surgical stress with more rapid recovery than enflurane.

Requirements for volatile inhalation anesthetics were reduced by thirty to fifty percent during the first 60 minutes of maintenance in patients administered anesthetic doses (above 130 mcg/kg) of ALFENTA as compared to patients given doses of 4-5 mg/kg thiopental for anesthetic induction. At anesthetic induction dosages, ALFENTA provides a deep level of anesthesia during the first hour of anesthetic maintenance and provides attenuation of the hemodynamic response during intubation and incision.

Following an anesthetic induction dose of ALFENTA, requirements for ALFENTA infusion are reduced by 30 to 50% for the first hour of maintenance.

Patients with compromised liver function and those over 65 years of age have been found to have reduced plasma clearance and extended terminal elimination for ALFENTA, which may prolong postoperative recovery. Repeated or continuous administration of ALFENTA produces increasing plasma concentrations and an accumulation of the drug, particularly in patients with reduced plasma clearance.

Bradycardia may be seen in patients administered ALFENTA. The incidence and degree of bradycardia may be more pronounced when ALFENTA is administered in conjunction with non-vagolytic neuromuscular blocking agents or in the absence of anticholinergic agents such as atropine.

Administration of intravenous diazepam immediately prior to or following high doses of ALFENTA has been shown to produce decreases in blood pressure that may be secondary to vasodilation; recovery may also be prolonged.

Patients administered doses up to 200 mcg/kg of ALFENTA have shown no significant increase in histamine levels and no clinical evidence of histamine release.

Skeletal muscle rigidity is related to the dose and speed of administration of ALFENTA. Muscular rigidity will occur with an immediate onset following anesthetic induction dosages. Preventative measures (see WARNINGS) may reduce the rate and severity.

The duration and degree of respiratory depression and increased airway resistance usually increase with dose, but have also been observed at lower doses. Although higher doses may produce apnea and a longer duration of respiratory depression, apnea may also occur at low doses.

During monitored anesthesia care (MAC), attention must be given to the respiratory effects of ALFENTA Injection. Decreased oxygen saturation, apnea, decreased respiratory rate, and upper airway obstruction can occur. (See WARNINGS)

INDICATIONS AND USAGE

ALFENTA (alfentanil hydrochloride) is indicated:

as an analgesic adjunct given in incremental doses in the maintenance of anesthesia with barbiturate/nitrous oxide/oxygen.
as an analgesic administered by continuous infusion with nitrous oxide/oxygen in the maintenance of general anesthesia.
as a primary anesthetic agent for the induction of anesthesia in patients undergoing general surgery in which endotracheal intubation and mechanical ventilation are required.
as the analgesic component for monitored anesthesia care (MAC).

SEE DOSAGE CHART FOR MORE COMPLETE INFORMATION ON THE USE OF ALFENTA.

CONTRAINDICATIONS

ALFENTA (alfentanil hydrochloride) is contraindicated in patients with known hypersensitivity to the drug or known intolerance to other opioid agonists.

WARNINGS

ALFENTA SHOULD BE ADMINISTERED ONLY BY PERSONS SPECIFICALLY TRAINED IN THE USE OF INTRAVENOUS AND GENERAL ANESTHETIC AGENTS AND IN THE MANAGEMENT OF RESPIRATORY EFFECTS OF POTENT OPIOIDS.

AN OPIOID ANTAGONIST, RESUSCITATIVE AND INTUBATION EQUIPMENT AND OXYGEN SHOULD BE READILY AVAILABLE.

BECAUSE OF THE POSSIBILITY OF DELAYED RESPIRATORY DEPRESSION, MONITORING OF THE PATIENT MUST CONTINUE WELL AFTER SURGERY.

ALFENTA (alfentanil hydrochloride) administered in initial dosages up to 20 mcg/kg may cause skeletal muscle rigidity, particularly of the truncal muscles. The incidence and severity of muscle rigidity is usually dose-related. Administration of ALFENTA at anesthetic induction dosages (above 130 mcg/kg) will consistently produce muscular rigidity with an immediate onset. The onset of muscular rigidity occurs earlier than with other opioids. ALFENTA may produce muscular rigidity that involves all skeletal muscles, including those of the neck and extremities. The incidence may be reduced by: 1) routine methods of administration of neuromuscular blocking agents for balanced opioid anesthesia; 2) administration of up to 1/4 of the full paralyzing dose of a neuromuscular blocking agent just prior to administration of ALFENTA at dosages up to 130 mcg/kg; following loss of consciousness, a full paralyzing dose of a neuromuscular blocking agent should be administered; or 3) simultaneous administration of ALFENTA and a full paralyzing dose of a neuromuscular blocking agent when ALFENTA is used in rapidly administered anesthetic dosages (above 130 mcg/kg).

The neuromuscular blocking agent used should be appropriate for the patient's cardiovascular status. Adequate facilities should be available for postoperative monitoring and ventilation of patients administered ALFENTA. It is essential that these facilities be fully equipped to handle all degrees of respiratory depression.

PATIENTS RECEIVING MONITORED ANESTHESIA CARE (MAC) SHOULD BE CONTINUOUSLY MONITORED BY PERSONS NOT INVOLVED IN THE CONDUCT OF THE SURGICAL OR DIAGNOSTIC PROCEDURE; OXYGEN SUPPLEMENTATION SHOULD BE IMMEDIATELY AVAILABLE AND PROVIDED WHERE CLINICALLY INDICATED; OXYGEN SATURATION SHOULD BE CONTINUOUSLY MONITORED; THE PATIENT SHOULD BE OBSERVED FOR EARLY SIGNS OF HYPOTENSION, APNEA, UPPER AIRWAY OBSTRUCTION AND/OR OXYGEN DESATURATION.

Severe and unpredictable potentiation of monoamine oxidase (MAO) inhibitors has been reported for other opioid analgesics, and rarely with alfentanil. Therefore when alfentanil is administered to patients who have received MAO inhibitors within 14 days, appropriate monitoring and ready availability of vasodilators and beta-blockers for the treatment of hypertension is recommended.

PRECAUTIONS

DELAYED RESPIRATORY DEPRESSION, RESPIRATORY ARREST, BRADYCARDIA, ASYSTOLE, ARRHYTHMIAS AND HYPOTENSION HAVE ALSO BEEN REPORTED. THEREFORE, VITAL SIGNS MUST BE MONITORED CONTINUOUSLY.

General

The initial dose of ALFENTA (alfentanil hydrochloride) should be appropriately reduced in elderly and debilitated patients. The effect of the initial dose should be considered in determining supplemental doses. In obese patients (more than 20% above ideal total body weight), the dosage of ALFENTA should be determined on the basis of lean body weight.

In one clinical trial, the dose of ALFENTA required to produce anesthesia, as determined by appearance of delta waves in EEG, was 40% lower in geriatric patients than that needed in healthy young patients.

In patients with compromised liver function and in geriatric patients, the plasma clearance of ALFENTA may be reduced and postoperative recovery may be prolonged.

Induction doses of ALFENTA should be administered slowly (over three minutes). Administration may produce loss of vascular tone and hypotension. Consideration should be given to fluid replacement prior to induction.

Diazepam administered immediately prior to or in conjunction with high doses of ALFENTA may produce vasodilation, hypotension and result in delayed recovery.

Bradycardia produced by ALFENTA may be treated with atropine. Severe bradycardia and asystole have been successfully treated with atropine and conventional resuscitative methods.

The hemodynamic effects of a particular muscle relaxant and the degree of skeletal muscle relaxation required should be considered in the selection of a neuromuscular blocking agent.

Following an anesthetic induction dose of ALFENTA, requirements for volatile inhalation anesthetics or ALFENTA infusion are reduced by 30 to 50% for the first hour of maintenance.

ALFENTA infusions should be discontinued at least 10-15 minutes prior to the end of surgery during general anesthesia. During administration of ALFENTA for Monitored Anesthesia Care (MAC), infusions may be continued to the end of the procedure.

Respiratory depression caused by opioid analgesics can be reversed by opioid antagonists such as naloxone. Because the duration of respiratory depression produced by ALFENTA may last longer than the duration of the opioid antagonist action, appropriate surveillance should be maintained. As with all potent opioids, profound analgesia is accompanied by respiratory depression and diminished sensitivity to CO2 stimulation which may persist into or recur in the postoperative period. Intraoperative hyperventilation may further alter postoperative response to CO2. Appropriate postoperative monitoring should be employed, particularly after infusions and large doses of ALFENTA, to ensure that adequate spontaneous breathing is established and maintained in the absence of stimulation prior to discharging the patient from the recovery area.

Head Injuries

ALFENTA should be used with caution in patients with head injury or increased intracranial pressure, due to the increased risk of respiratory depression. As with all opioids, ALFENTA may obscure the clinical course of patients with head injuries and should be used only if clinically indicated.

Impaired Respiration

ALFENTA should be used with caution in patients with pulmonary disease, decreased respiratory reserve or potentially compromised respiration. In such patients, opioids may additionally decrease respiratory drive and increase airway resistance. During anesthesia, this can be managed by assisted or controlled respiration.

Impaired Hepatic or Renal Function

In patients with liver or kidney dysfunction, ALFENTA should be administered with caution due to the importance of these organs in the metabolism and excretion of ALFENTA.

Drug Interactions

Both the magnitude and duration of central nervous system and cardiovascular effects may be enhanced when ALFENTA is administered in combination with other CNS depressants such as barbiturates, tranquilizers, opioids, or inhalation general anesthetics. Postoperative respiratory depression may be enhanced or prolonged by these agents. In such cases of combined treatment, the dose of one or both agents should be reduced. Limited clinical experience indicates that requirements for volatile inhalation anesthetics are reduced by 30 to 50% for the first sixty (60) minutes following ALFENTA induction.

The concomitant use of erythromycin with ALFENTA can significantly inhibit ALFENTA clearance and may increase the risk of prolonged or delayed respiratory depression.

Cimetidine reduces the clearance of ALFENTA. Therefore smaller ALFENTA doses will be required with prolonged administration and the duration of action of ALFENTA may be extended.

Perioperative administration of drugs affecting hepatic blood flow or enzyme function may reduce plasma clearance and prolong recovery.

Carcinogenesis, Mutagenesis and Impairment of Fertility

No long-term animal studies of ALFENTA have been performed to evaluate carcinogenic potential. No structural chromosome mutations were produced in the in vivo micronucleus test in female rats at single intravenous doses of ALFENTA as high as 20 mg/kg body weight (approximately 40 times the upper human dose), equivalent to a dose of 103 mg/m^2 body surface area. No dominant lethal mutations were produced in the in vivo dominant lethal test in male and female mice at the maximum intravenous dose of 20 mg/kg (60 mg/m^2). No mutagenic activity was revealed in the in vitro Ames Salmonella typhimurium test, with and without metabolic activation.

Pregnancy Category C

ALFENTA has been shown to have an embryocidal effect in rats and rabbits when given in doses 2.5 times the upper human dose for a period of 10 days to over 30 days. These effects could have been due to maternal toxicity (decreased food consumption with increased mortality) following prolonged administration of the drug.

No evidence of teratogenic effects has been observed after administration of ALFENTA in rats or rabbits.

There are no adequate and well-controlled studies in pregnant women. ALFENTA should be used during pregnancy only if the potential benefit justifies the potential risk to the fetus.

Labor and Delivery

There are insufficient data to support the use of ALFENTA in labor and delivery. Placental transfer of the drug has been reported; therefore, use in labor and delivery is not recommended.

Nursing Mothers

In one study of nine women undergoing postpartum tubal ligation, significant levels of ALFENTA were detected in colostrum four hours after administration of 60 mcg/kg of ALFENTA, with no detectable levels present after 28 hours. Caution should be exercised when ALFENTA is administered to a nursing woman.

Pediatric Use

Adequate data to support the use of ALFENTA in children under 12 years of age are not presently available.

ADVERSE REACTIONS

The most common adverse reactions of opioids are respiratory depression and skeletal muscle rigidity, particularly of the truncal muscles. ALFENTA may produce muscular rigidity that involves the skeletal muscles of the neck and extremities. See CLINICAL PHARMACOLOGY, WARNINGS, and PRECAUTIONS on the management of respiratory depression and skeletal muscle rigidity.

The adverse experience profile from 696 patients receiving ALFENTA for Monitored Anesthesia Care (MAC) is similar to the profile established with ALFENTA during general anesthesia. Respiratory events reported during MAC included hypoxia, apnea, and bradypnea. Other adverse events reported by patients receiving ALFENTA for MAC, in order of decreasing frequency, were nausea, hypotension, vomiting, pruritus, confusion, somnolence and agitation.

The following adverse reaction information is derived from controlled and open clinical trials in 785 patients who received intravenous ALFENTA during induction and maintenance of general anesthesia. The controlled trials included treatment comparisons with fentanyl, thiopental sodium, enflurane, saline placebo and halothane. The incidence of certain side effects is influenced by the type of use, e.g., chest wall rigidity has a higher reported incidence in clinical trials of alfentanil induction, and by the type of surgery, e.g., nausea and vomiting have a higher reported incidence in patients undergoing gynecologic surgery. The overall reports of nausea and vomiting with ALFENTA were comparable to fentanyl.

Incidence Greater than 1% - Probably Causally Related (Derived from clinical trials)

Gastrointestinal: | nausea (28%), vomiting (18%)
Cardiovascular: | arrhythmia, bradycardia (14%), hypertension (18%), hypotension (10%), tachycardia (12%)
Musculoskeletal: | chest wall rigidity (17%), skeletal muscle movements [Incidence 3% to 9% All others 1% to 3%]
Respiratory: | apnea, postoperative respiratory depression
Central Nervous System: | blurred vision, dizziness, sleepiness/postoperative sedation

Incidence Less than 1% - Probably Causally Related (Derived from clinical trials)

Adverse events reported in post-marketing surveillance, not seen in clinical trials, are italicized.

Body as a whole: | anaphylaxis
Central Nervous System: | headache [Incidence 0.3% to 1%] , myoclonic movements, postoperative confusion, postoperative euphoria, shivering
Dermatological: | itching, urticaria*
Injection Site: | pain
Musculoskeletal: | skeletal muscle rigidity of neck and extremities
Respiratory: | bronchospasm, hypercarbia, laryngospasm

DRUG ABUSE AND DEPENDENCE

CONTROLLED SUBSTANCE

ALFENTA (alfentanil hydrochloride) is a Schedule II controlled drug substance that can produce drug dependence of the morphine type and therefore has the potential for being abused.

ABUSE

Opioid analgesics have been associated with abuse and dependence in health care providers and others with ready access to such drugs. ALFENTA should be handled accordingly.

OVERDOSAGE

Overdosage would be manifested by extension of the pharmacological actions of ALFENTA (alfentanil hydrochloride) (see CLINICAL PHARMACOLOGY) as with other potent opioid analgesics. No experience of overdosage with ALFENTA was reported during clinical trials. The intravenous LD50 of ALFENTA is 43-51 mg/kg in rats, 72-74 mg/kg in mice, 72-82 mg/kg in guinea pigs and 60-88 mg/kg in dogs. Intravenous administration of an opioid antagonist such as naloxone should be employed as a specific antidote to manage respiratory depression.

The duration of respiratory depression following overdosage with ALFENTA may be longer than the duration of action of the opioid antagonist. Administration of an opioid antagonist should not preclude immediate establishment of a patent airway, administration of oxygen, and assisted or controlled ventilation as indicated for hypoventilation or apnea. If respiratory depression is associated with muscular rigidity, a neuromuscular blocking agent may be required to facilitate assisted or controlled ventilation. Intravenous fluids and vasoactive agents may be required to manage hemodynamic instability.

DOSAGE AND ADMINISTRATION

The dosage of ALFENTA (alfentanil hydrochloride) should be individualized and titrated to the desired effect in each patient according to body weight, physical status, underlying pathological condition, use of other drugs, and type and duration of surgical procedure and anesthesia. In obese patients (more than 20% above ideal total body weight), the dosage of ALFENTA should be determined on the basis of lean body weight. The dose of ALFENTA should be reduced in elderly or debilitated patients (see PRECAUTIONS).

Vital signs should be monitored routinely.

See Dosage Guidelines for the use of ALFENTA: 1) by incremental injection as an analgesic adjunct to anesthesia with barbiturate/nitrous oxide/oxygen for short surgical procedures (expected duration of less than one hour); 2) by continuous infusion as a maintenance analgesic with nitrous oxide/oxygen for general surgical procedures; and 3) by intravenous injection in anesthetic doses for the induction of anesthesia for general surgical procedures with a minimum expected duration of 45 minutes; and 4) by intravenous injection as the analgesic component for monitored anesthesia care (MAC).

DOSAGE GUIDELINES
DOSAGE SHOULD BE INDIVIDUALIZED AND TITRATED
FOR USE DURING GENERAL ANESTHESIA
SPONTANEOUSLY BREATHING/ASSISTED VENTILATION | Induction of Analgesia: 8-20 mcg/kg Maintenance of Analgesia: 3-5 mcg/kg q 5-20 min or 0.5 to 1 mcg/kg/min Total dose: 8-40 mcg/kg
ASSISTED OR CONTROLLED VENTILATION
Incremental Injection (To attenuate response to laryngoscopy and intubation) | Induction of Analgesia: 20-50 mcg/kg Maintenance of Analgesia: 5-15 mcg/kg q 5-20 min Total dose: Up to 75 mcg/kg
Continuous Infusion (To provide attenuation of response to intubation and incision) | Infusion rates are variable and should be titrated to the desired clinical effect. SEE INFUSION DOSAGE GUIDELINES BELOW. Induction of Analgesia: 50-75 mcg/kg Maintenance of Analgesia: 0.5 to 3 mcg/kg/min (Average rate 1 to 1.5 mcg/kg/min) Total dose: Dependent on duration of procedure
Anesthetic Induction | Induction of Anesthesia: 130-245 mcg/kg Maintenance of Anesthesia: 0.5 to 1.5 mcg/kg/min or general anesthetic Total dose: Dependent on duration of procedure At these doses, truncal rigidity should be expected and a muscle relaxant should be utilized. Administer slowly (over 3 minutes). Concentration of inhalation agents reduced by 30-50% for initial hour.
MONITORED ANESTHESIA CARE (MAC) (For sedated and responsive, spontaneously breathing patients) | Induction of MAC: 3-8 mcg/kg Maintenance of MAC: 3-5 mcg/kg q 5-20 min or 0.25 to 1 mcg/kg/min Total dose: 3-40 mcg/kg

INFUSION DOSAGE

Continuous Infusion: 0.5-3 mcg/kg/min administered with nitrous oxide/oxygen in patients undergoing general surgery. Following an anesthetic induction dose of ALFENTA, infusion rate requirements are reduced by 30-50% for the first hour of maintenance.

Changes in vital signs that indicate a response to surgical stress or lightening of anesthesia may be controlled by increasing the alfentanil to a maximum of 4 mcg/kg/min and/or administration of bolus doses of 7 mcg/kg. If changes are not controlled after three bolus doses given over a five minute period, a barbiturate, vasodilator, and/or inhalation agent should be used. Infusion rates should always be adjusted downward in the absence of these signs until there is some response to surgical stimulation.

Rather than an increase in infusion rate, 7 mcg/kg bolus doses of ALFENTA or a potent inhalation agent should be administered in response to signs of lightening of anesthesia within the last 15 minutes of surgery. ALFENTA infusion should be discontinued at least 10-15 minutes prior to the end of surgery.

Usage in Children

Clinical data to support the use of ALFENTA in patients under 12 years of age are not presently available. Therefore, such use is not recommended.

Premedication

The selection of preanesthetic medications should be based upon the needs of the individual patient.

Neuromuscular Blocking Agents

The neuromuscular blocking agent selected should be compatible with the patient's condition, taking into account the hemodynamic effects of a particular muscle relaxant and the degree of skeletal muscle relaxation required (see CLINICAL PHARMACOLOGY, WARNINGS and PRECAUTIONS sections).

In patients administered anesthetic (induction) dosages of ALFENTA, it is essential that qualified personnel and adequate facilities are available for the management of intraoperative and postoperative respiratory depression.

Also see WARNINGS and PRECAUTIONS sections.

For purposes of administering small volumes of ALFENTA accurately, the use of a tuberculin syringe or equivalent is recommended.

The physical and chemical compatibility of ALFENTA have been demonstrated in solution with normal saline, 5% dextrose in normal saline, 5% dextrose in water and Lactated Ringers. Clinical studies of ALFENTA infusion have been conducted with ALFENTA diluted to a concentration range of 25 mcg/mL to 80 mcg/mL.

As an example of the preparation of ALFENTA for infusion, 20 mL of ALFENTA added to 230 mL of diluent provides 40 mcg/mL solution of ALFENTA.

Parenteral drug products should be inspected visually for particulate matter and discoloration prior to administration, whenever solution and container permit.

SAFETY AND HANDLING

ALFENTA (alfentanil hydrochloride) is supplied in individually sealed dosage forms which pose no known risk to health-care providers having incidental contact. Accidental dermal exposure to ALFENTA should be treated by rinsing the affected area with water.

Protect from light. Storage: Store at 20° to 25°C (68° to 77°F). [See USP Controlled Room Temperature].

HOW SUPPLIED

ALFENTA (alfentanil hydrochloride) Injection for intravenous use. Each mL Contains: Active: Alfentanil base 500 mcg. Inactives: Sodium Chloride 9 mg and WFI Q.S ALFENTA Injection is available as:

NDC 11098-060-02, 2 mL Ampule in packages of 10
NDC 11098-060-05, 5 mL Ampule in packages of 10
NDC 11098-060-10, 10 mL Ampule in packages of 5
NDC 11098-060-20, 20 mL Ampule in packages of 5

U.S. Patent No. 4,167,574
May 1995, November 1995

TAYLOR PHARMACEUTICALS
AN AKORN COMPANY

Decatur, IL 62522

AFA0N Rev. 06/05